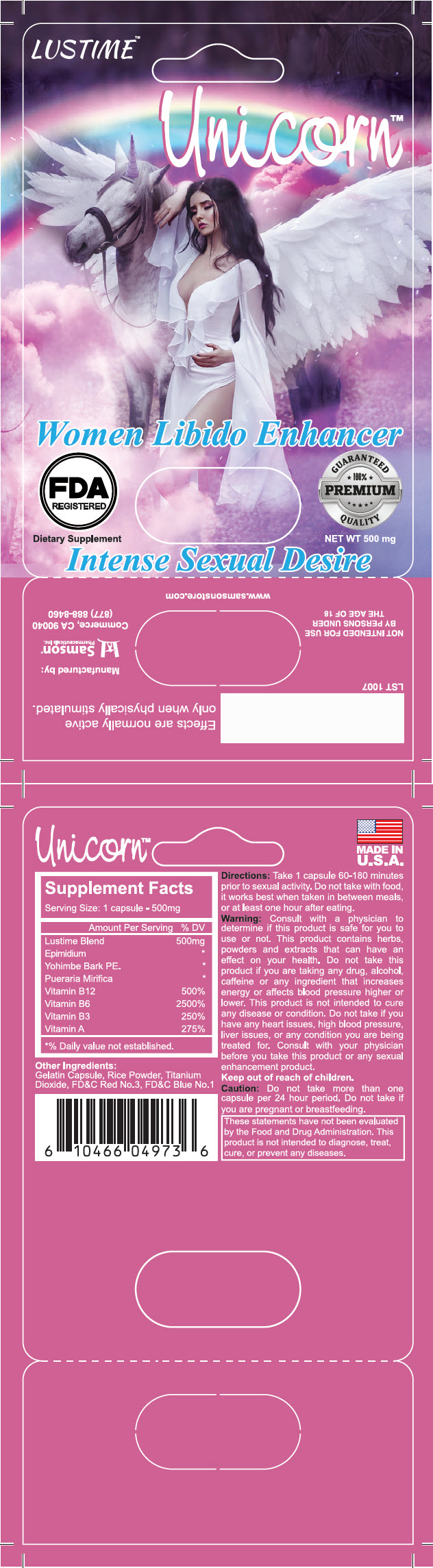 DRUG LABEL: Lustime Unicorn
NDC: 20146-1023 | Form: CAPSULE
Manufacturer: SAMSON PHARMACEUTICAL
Category: other | Type: DIETARY SUPPLEMENT
Date: 20200212

ACTIVE INGREDIENTS: PYRIDOXINE 50 mg/1 1; NIACIN 50 mg/1 1; CYANOCOBALAMIN 0.03 mg/1 1; VITAMIN A 50 mg/1 1
INACTIVE INGREDIENTS: PUERARIA CANDOLLEI VAR. MIRIFICA ROOT; EPIMEDIUM WUSHANENSE WHOLE; YOHIMBINE; WHITE RICE

Lustime Unicorn

STATEMENT OF IDENTITY

Supplement Facts
Serving Size: 1 capsule - 500mg
Amount Per Serving % DV
Lustime Blend | 500mg
Epimidium | [% Daily value not established.]
Yohimbe Bark PE.
Pueraria Mirifica
Vitamin B12 | 500%
Vitamin B6 | 2500%
Vitamin B3 | 250%
Vitamin A | 275%

Other Ingredients:

Gelatin Capsule, Rice Powder, Titanium Dioxide, FD&C Red No.3, FD&C Blue No.1

Directions

Take 1 capsule 60-180 minutes prior to sexual activity. Do not take with food, it works best when taken in between meals, or at least one hour after eating.

Warning

Consult with a physician to determine if this product is safe for you to use or not. This product contains herbs, powders and extracts that can have an effect on your health. Do not take this product if you are taking any drug, alcohol, caffeine or any ingredient that increases energy or affects blood pressure higher or lower. This product is not intended to cure any disease or condition. Do not take if you have any heart issues, high blood pressure, liver issues, or any condition you are being treated for. Consult with your physician before you take this product or any sexual enhancement product.

Keep out of reach of children.

Caution

Do not take more than one capsule per 24 hour period. Do not take if you are pregnant or breastfeeding.

HEALTH CLAIM

These statements have not been evaluated by the Food and Drug Administration. This product is not intended to diagnose, treat, cure, or prevent any diseases.

Effects are normally active only when physically stimulated.

NOT INTENDED FOR USE
BY PERSONS UNDER
THE AGE OF 18

PRINCIPAL DISPLAY PANEL - 500 mg Capsule Blister Pack

LUSTIME™

Unicorn™

Women Libido Enhancer

FDA
REGISTERED

GUARANTEED
100%
PREMIUM
QUALITY

Dietary Supplement

NET WT 500 mg

Intense Sexual Desire